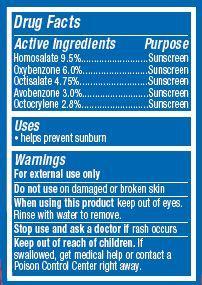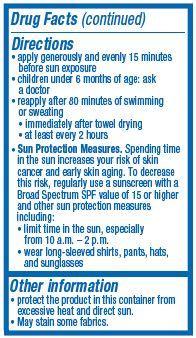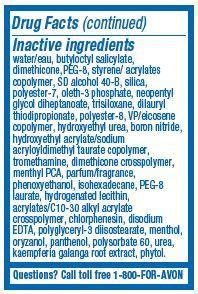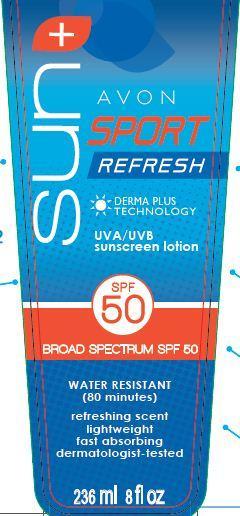 DRUG LABEL: Avon Sun Sport
NDC: 10096-0313 | Form: LOTION
Manufacturer: New Avon LLC
Category: otc | Type: HUMAN OTC DRUG LABEL
Date: 20160219

ACTIVE INGREDIENTS: HOMOSALATE 95 mg/1 mL; OXYBENZONE 60 mg/1 mL; OCTISALATE 47.5 mg/1 mL; AVOBENZONE 30 mg/1 mL; OCTOCRYLENE 28 mg/1 mL

Active ingredients
HOMOSALATE 9.5%..................

OXYBENZONE 6.0%.....................

OCTISALATE 4.75%.....................

AVOBENZONE 3.0%...................

OCTOCRYLENE 2.8%..................

Purpose
.................................Sunscreen

.................................Sunscreen

.................................Sunscreen

.................................Sunscreen

.................................Sunscreen

Uses
• helps prevent sunburn

Warnings
For external use only

Do not use on damaged or broken skin

When using this product

- keep out of eyes. Rinse with water to remove.

Stop use and ask a doctor if rash occurs

Keep out of reach of children.

If swallowed, get medical help or contact a Poison Control Center right away.

Directions
• apply generously and evenly 15 minutes before sun exposure
• children under 6 months of age: ask a doctor
• reapply after 80 minutes of swimming or sweating
• immediately after towel drying

• at least every 2 hours

• Sun Protection Measures. Spending time in the sun increases your risk of skin cancer and early skin aging. To decrease this risk, regularly use a sunscreen with a Broad Spectrum SPF value of 15 or higher and other sun protection measures including:
• limit time in the sun, especially from 10 a.m. – 2 p.m.
• wear long-sleeved shirts, pants, hats, and sunglasses

Other information

• protect the product in this container from excessive heat and direct sun

• May stain some fabrics.

Inactive Ingredients:
water/eau, butyloctyl salicylate, dimethicone, PEG-8, styrene/ acrylates copolymer, SD alcohol 40-B, silica, polyester-7, oleth-3 phosphate, neopentyl glycol diheptanoate, trisiloxane, dilauryl thiodipropionate, polyester-8, VP/eicosene copolymer, hydroxyethyl urea, boron nitride,
hydroxyethyl acrylate/sodium acryloyldimethyl taurate copolymer, tromethamine, dimethicone crosspolymer, menthyl PCA, parfum/fragrance,
phenoxyethanol, isohexadecane, PEG-8 laurate, hydrogenated lecithin, acrylates/C10-30 alkyl acrylate crosspolymer, chlorphenesin, disodium EDTA, polyglyceryl-3 diisostearate, menthol, oryzanol, panthenol, polysorbate 60, urea, kaempferia galanga root extract, phytol.

Questions?
Call toll free 1-800-FOR-AVON